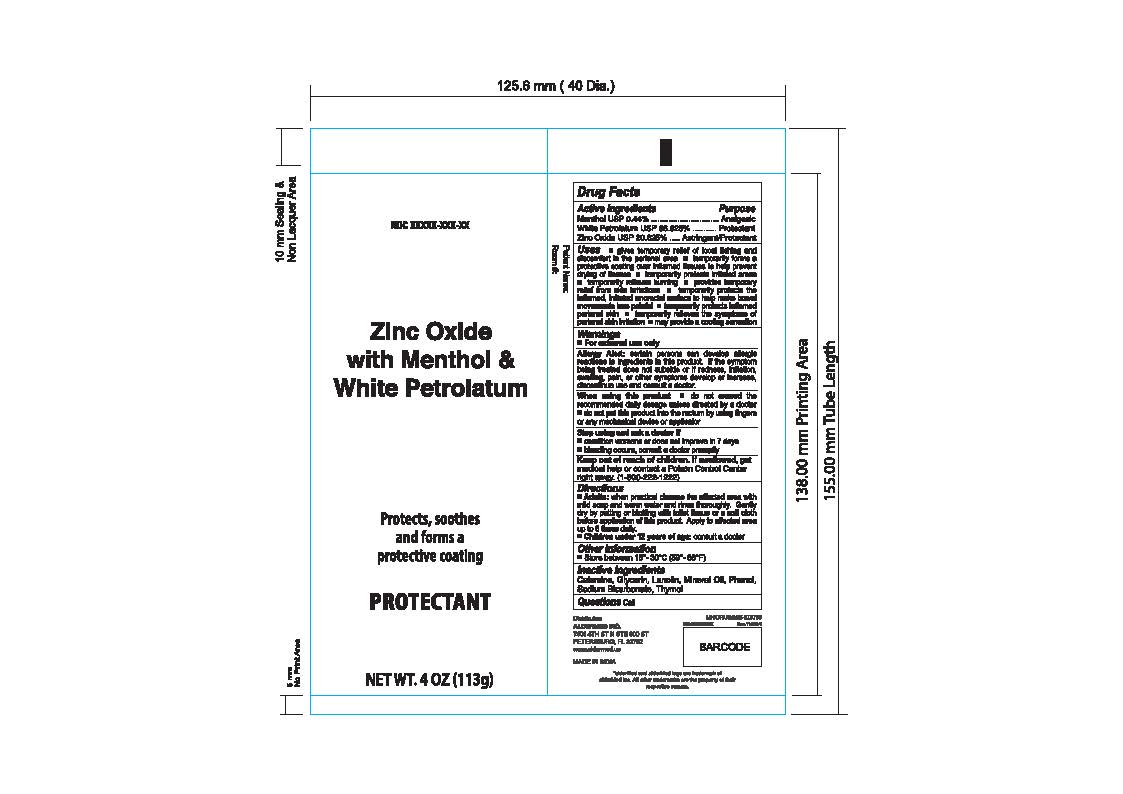 DRUG LABEL: Zinc Oxide with Menthol and White Petrolatum
NDC: 87236-008 | Form: OINTMENT
Manufacturer: Aldermed Inc.
Category: otc | Type: HUMAN OTC DRUG LABEL
Date: 20260123

ACTIVE INGREDIENTS: MENTHOL 0.44 g/100 g; ZINC OXIDE 20.625 g/100 g; WHITE PETROLATUM 66.625 g/100 g
INACTIVE INGREDIENTS: FERRIC OXIDE RED; GLYCERIN; PHENOL; LANOLIN; MINERAL OIL; SODIUM BICARBONATE; THYMOL

Zinc Oxide with Menthol & White Petrolatum

Active Ingredient

Menthol 0.44%

Zinc Oxide 20.625%

White Petrolatum USP 66.625%

Purpose

Analgesic

External Analgesic

Astringent/Protectant

Uses

■ gives temporary relief of local itching and discomfort in the perianal area

■ temporarily forms a protective coating over inflamed tissues to help prevent drying of tissues

■ temporarily protects irritated areas

■ temporarily relieves burning

■ provides temporary relief from skin irritations

■ temporarily protects the inflamed, irritated anorectal surface to help make bowel movements less painful

■ temporarily protects inflamed perianal skin

■ temporarily relieves the symptoms of perianal skin irritation

■ may provide a cooling sensation

Warnings

For external use only

Allergy Alert: certain persons can develop allergic reactions to ingredients in this product. If the symptom being treated does not subside or if redness, irritation, swelling, pain, or other symptoms develop or increase, discontinue use and consult a doctor.

When using this product

■ do not exceed the recommended daily dosage unless directed by a doctor
■ do not put this product into the rectum by using fingers or any mechanical device or applicator

Stop use and ask a doctor if

■ condition worsens or does not improve in 7 days
■ bleeding occurs, consult a doctor promptly

Keep Out Of Reach Of Children

If swallowed, get medical help or contact a Poison Control Center right away. (1-800-222-1222)

Directions

■ Adults: when practical cleanse the affected area with mild soap and warm water and rinse thoroughly. Gently dry by patting or blotting with toilet tissue or a soft cloth before application of this product. Apply to affected area up to 6 times daily.

■ Children under 12 years of age: consult a doctor

Other Information

• Store at room temperature 15º-30º C (59º-86º F)

Inactive Ingredients

Calamine, Glycerine, Lanolin, Mineral Oil, Phenol, Sodium Bicarbonate, Thymol

Questions?

Gopaldas Visram and Company Limited.

Address - A/327, TTC Industrial Area,

MIDC Mahape, Navi Mumbai,

Maharashtra 400710, India